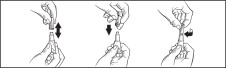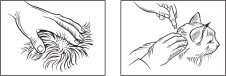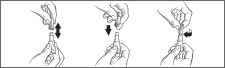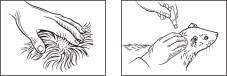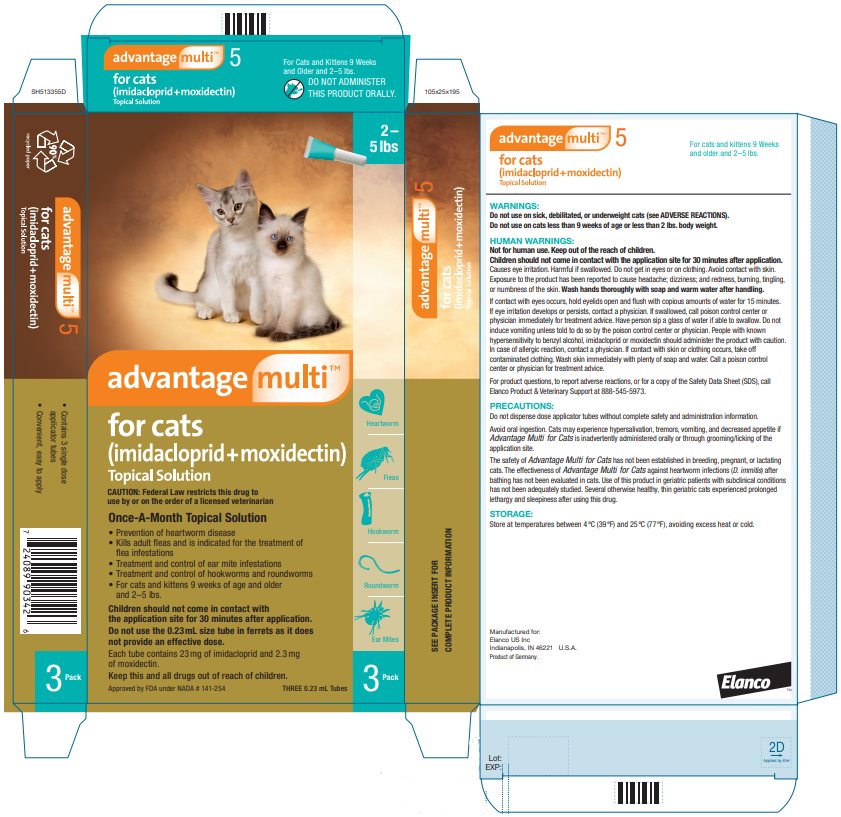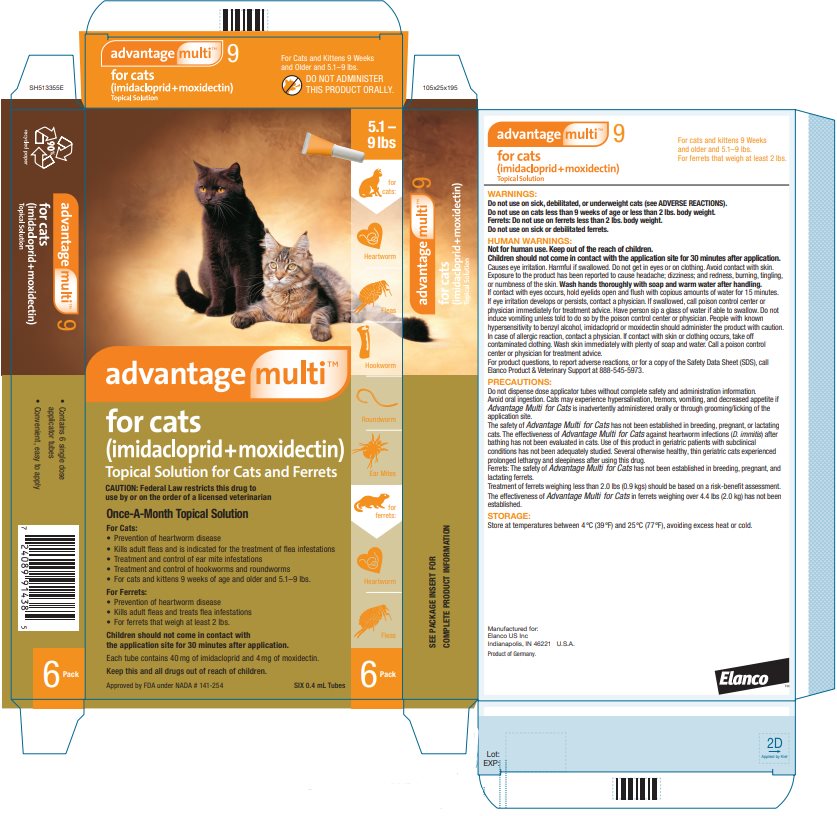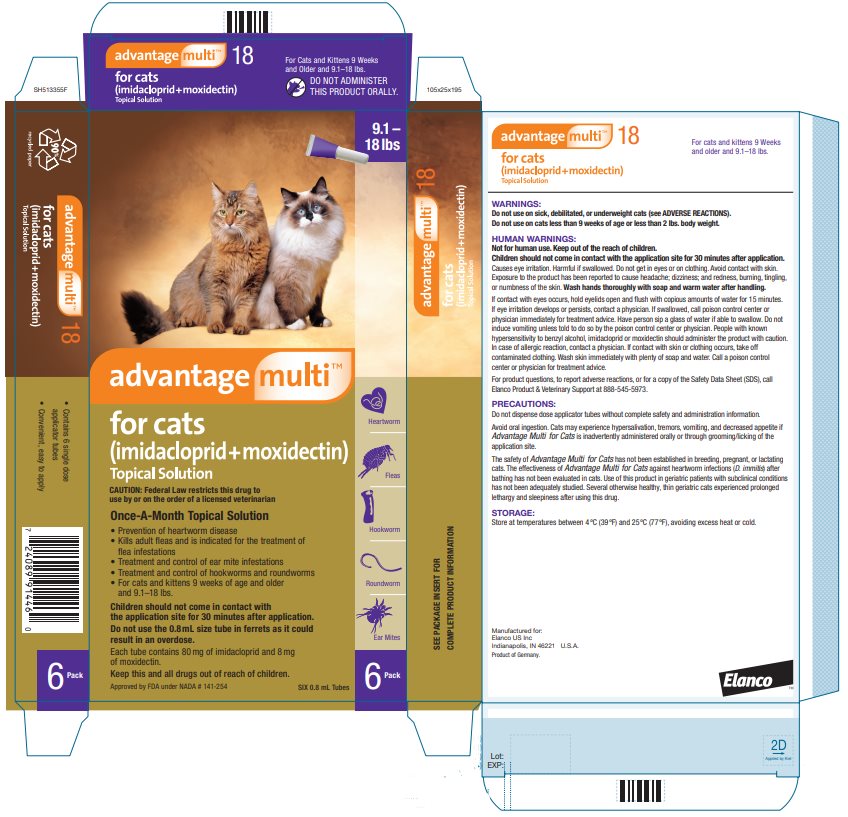 DRUG LABEL: ADVANTAGE MULTI FOR CATS
NDC: 58198-0053 | Form: SOLUTION
Manufacturer: Elanco US Inc.
Category: animal | Type: PRESCRIPTION ANIMAL DRUG LABEL
Date: 20251029

ACTIVE INGREDIENTS: IMIDACLOPRID 100 mg/1 mL; MOXIDECTIN 10 mg/1 mL

ElancoTM
advantage multi™
for cats
(imidacloprid+moxidectin)
Topical Solution

Once-a-month topical solution for cats for the prevention of heartworm disease, kills adult fleas, is indicated for the treatment of flea infestations, as well as the treatment and control of ear mite infestations and intestinal parasite infections in cats and kittens 9 weeks of age and older and that weigh at least 2 lbs.

Once-a-month topical solution for ferrets for the prevention of heartworm disease, kills adult fleas, and is indicated for the treatment of flea infestations. Indicated for ferrets that weigh at least 2 lbs.

CAUTION:

Federal Law restricts this drug to use by or on the order of a licensed veterinarian.

DESCRIPTION:

Advantage Multi for Cats (10 % imidacloprid + 1 % moxidectin) is a colorless to yellow ready-to-use solution packaged in single-dose applicator tubes for topical treatment of cats. The formulation and dosage schedule are designed to provide a minimum of 4.5 mg/lb (10.0 mg/kg) imidacloprid and 0.45 mg/lb (1.0 mg/kg) moxidectin based on body weight.

Imidacloprid is a chloronicotinyl nitroguanidine insecticide. The chemical name of imidacloprid is 1-[(6-Chloro-3-pyridinyl)methyl]-N-nitro-2-imidazolidinimine. Moxidectin is a semisynthetic macrocyclic lactone endectocide derived from the actinomycete Streptomycetes cyaneogriseus noncyanogenus. The chemical name of moxidectin is [6R, 23E, 25S(E)]-5-0-Demethyl-28-deoxy-25-(1,3-dimethyl-1-butenyl)-6,28-epoxy-23-(methoxyimino) milbemycin B.

INDICATIONS:

Advantage Multi for Cats is indicated for the prevention of heartworm disease caused by Dirofilaria immitis. Advantage Multi for Cats kills adult fleas (Ctenocephalides felis) and is indicated for the treatment of flea infestations. Advantage Multi for Cats is also indicated for the treatment and control of ear mite (Otodectes cynotis) infestations and the following intestinal parasites:

Intestinal Parasite |  | Intestinal Stage
Intestinal Parasite |  | Adult | Immature Adult | Fourth Stage Larvae
Hookworm Species | Ancylostoma tubaeforme | X | X | X
Roundworm Species | Toxocara cati | X |  | X

WARNINGS:

Do not use on sick, debilitated, or underweight cats (See ADVERSE REACTIONS).

Do not use on cats less than 9 weeks of age or less than 2 lbs. body weight.

HUMAN WARNINGS:

Not for human use. Keep out of the reach of children.

Children should not come in contact with the application site for 30 minutes after application.

Causes eye irritation. Harmful if swallowed. Do not get in eyes or on clothing. Avoid contact with skin. Exposure to the product has been reported to cause headache; dizziness; and redness, burning, tingling, or numbness of the skin.

Wash hands thoroughly with soap and warm water after handling.

If contact with eyes occurs, hold eyelids open and flush with copious amounts of water for 15 minutes. If eye irritation develops or persists, contact a physician. If swallowed, call poison control center or physician immediately for treatment advice. Have person sip a glass of water if able to swallow. Do not induce vomiting unless told to do so by the poison control center or physician. People with known hypersensitivity to benzyl alcohol, imidacloprid or moxidectin should administer the product with caution. In case of allergic reaction, contact a physician. If contact with skin or clothing occurs, take off contaminated clothing. Wash skin immediately with plenty of soap and water. Call a poison control center or physician for treatment advice.

The Safety Data Sheet (SDS) provides additional occupational safety information. For product questions, to report adverse reactions, or for a copy of the Safety Data Sheet (SDS), call Elanco Product & Veterinary Support at 888-545-5973.

PRECAUTIONS:

Do not dispense dose applicator tubes without complete safety and administration information.

Avoid oral ingestion. Cats may experience hypersalivation, tremors, vomiting and decreased appetite if Advantage Multi for Cats is inadvertently administered orally or through grooming/licking of the application site.

The safety of Advantage Multi for Cats has not been established in breeding, pregnant, or lactating cats.

The effectiveness of Advantage Multi for Cats against heartworm infections (D. immitis) after bathing has not been evaluated in cats.

Use of this product in geriatric patients with subclinical conditions has not been adequately studied. Several otherwise healthy, thin geriatric cats experienced prolonged lethargy and sleepiness after using this drug.

(See ADVERSE REACTIONS.)

ADVERSE REACTIONS:

Field Study: Following treatment with Advantage Multi for Cats or an active control, cat owners reported the following post-treatment reactions:

OBSERVATION | Advantage Multi n = 113 | Active Control n = 38
Lethargy (protracted sleeping, poorly responsive) | 3 cats* (2.7 %) | None observed
Behavioral changes (e.g., agitated, excessive grooming, hiding, pacing, spinning) | 9 cats (8.0 %) | 1 cat (2.6 %)
Discomfort (e.g., scratching, rubbing, head-shaking) | 5 cats (4.4 %) | None observed
Hypersalivation (within 1 hour after treatment) | 3 cats (2.7 %) | None observed
Polydipsia | 3 cats (2.7 %) | None observed
Coughing and gagging | 1 cat (0.9 %) | None observed
* These three cats were from the same household and included one 13-yr-old cat in good health, one 15-yr-old FIV positive cat in good health, and one 15-yr-old, underweight cat in fair health. Lethargy was noted for 24 to 36 hrs after the first treatment only; one cat was unsteady at 48 hrs. These cats were not on other medications.

During another field study, a 16-year-old cat with renal disease slept in the same place without moving for two days following application.

(See PRECAUTIONS.)

Laboratory Effectiveness Studies: Advantage Multi for Cats was administered at the recommended dose to 215 cats in 20 effectiveness studies. One random-sourced cat exhibited signs consistent with either moxidectin toxicity or viral respiratory disease and died 26 hours after product application; necropsy findings were inconclusive as to the cause of death. A second cat that became ill 3 days after application of Advantage Multi for Cats responded to treatment for respiratory infection and completed the study. A third cat became ill on day 3 and died with signs and lesions attributable to panleukopenia on day 7 after moxidectin application.

Post-Approval Experience: The following adverse events are based on post-approval adverse drug experience reporting. Not all adverse reactions are reported to FDA CVM. It is not always possible to reliably estimate the adverse event frequency or establish a causal relationship to product exposure using this data. The following adverse events in cats are listed in decreasing order of reporting frequency: hypersalivation, depression/lethargy, application site reactions (alopecia, pruritus, lesions, and erythema), decreased appetite, vomiting, hyperactivity, ataxia, trembling, and behavior disorder (hiding).

In some cases death has been reported.

In humans, ocular and dermal irritation, nausea, numbness or tingling of the mouth and lips, anaphylaxis, pruritus, vomiting, and tongue/taste abnormalities have been reported following exposure to this product.

CONTACT INFORMATION:

For product questions, to report adverse reactions, or for a copy of the Safety Data Sheet (SDS), call Elanco Product & Veterinary Support at 888-545-5973.

For additional information about reporting adverse drug experiences for animal drugs, contact FDA at 1-888-FDA-VETS or http://www.fda.gov/reportanimalae.

DOSAGE AND ADMINISTRATION:

The recommended minimum dose is 4.5 mg/lb (10.0 mg/kg) imidacloprid and 0.45 mg/lb (1.0 mg/kg) moxidectin, once a month, by topical administration.

Do not apply to irritated skin.

1. Remove one dose applicator tube from the package. As specified in the following table, administer the entire contents of the Advantage Multi for Cats tube that correctly corresponds with the body weight of the cat.

Cat (lbs.) | Advantage Multi For Cats | Volume (mL) | Imidacloprid (mg) | Moxidectin (mg)
2–5 | Advantage Multi 5 | 0.23 | 23 | 2.3
5.1–9 | Advantage Multi 9 | 0.4 | 40 | 4
9.1–18* | Advantage Multi 18 | 0.8 | 80 | 8
* Cats over 18 lbs. should be treated with the appropriate combination of Advantage Multi for Cats tubes.

2. While holding the tube in an upright position, remove the cap from the tube.
3. Turn the cap over and push the other end of cap onto the tip of the tube.
4. Twist the cap to break the seal and then remove cap from the tube.
5. Part the hair on the back of the cat's neck at the base of the head, until the skin is visible. Place the tip of the tube on the skin and apply the entire contents directly on the exposed skin. Lift tube away from skin before releasing pressure on tube.

Do not get this product in the cat's mouth or eyes or allow the cat to lick the application site for 30 minutes. Treatment at the base of the head will minimize the opportunity for ingestion by grooming. In households with multiple pets, keep animals separated to prevent licking of the application site.

Stiff, matted hair or a damp, oily appearance of the hair may be observed at the application site on some cats. This is temporary and does not affect the safety and effectiveness of the product.

Heartworm Prevention: For prevention of heartworm disease, Advantage Multi for Cats should be administered at one-month intervals. Advantage Multi for Cats may be administered year-around or at a minimum should start one month before the first expected exposure to mosquitoes and should continue at monthly intervals until one month after the last exposure to mosquitoes. If a dose is missed and a 30-day interval between doses is exceeded, administer Advantage Multi for Cats immediately and resume the monthly dosing schedule. When replacing another heartworm preventative product in a heartworm prevention program, the first treatment with Advantage Multi for Cats should be given within one month of the last dose of the former medication. At the discretion of the veterinarian, cats older than 6 months of age may be tested to determine the presence of existing heartworm infection before treatment with Advantage Multi for Cats (See ADVERSE REACTIONS – Post-Approval Experience).

Flea Treatment: For the treatment of flea infestations, Advantage Multi for Cats should be administered at one-month intervals. If the cat is already infested with fleas when the first dose of Advantage Multi for Cats is administered, adult fleas on the cat will be killed. However, re-infestation from the emergence of pre-existing pupae in the environment may continue to occur for six weeks or longer after treatment is initiated. Cats treated with imidacloprid, including those with pre-existing flea allergy dermatitis have shown clinical improvement as a direct result of elimination of fleas from the cat.

Ear Mite Treatment: For the treatment of ear mites (Otodectes cynotis), Advantage Multi for Cats should be administered once as a single topical dose. Monthly use of Advantage Multi for Cats will control any subsequent ear mite infestations.

Intestinal Nematode Treatment: For the treatment and control of intestinal hookworm infections caused by Ancylostoma tubaeforme (adults, immature adults and fourth stage larvae) and roundworm infections caused by Toxocara cati (adults and fourth stage larvae), Advantage Multi for Cats should be administered once as a single topical dose.

ANIMAL SAFETY:

Studies in Kittens: Advantage Multi for Cats was topically applied at 0, 1, 3, and 5X the maximum dose to 48 healthy 9-week-old kittens on days 0, 28, and 56. Lethargy was observed in 1 kitten from the 3X group and 1 from the 5X group on the day after initial treatment; the kitten from the 3X group was also disoriented and ataxic. One kitten from the 3X group had a slow pupillary light response two days after treatment and one had tremors the day after treatment. Hypersalivation was seen in one kitten from the 5X group approximately six hours post-treatment. One kitten from the 3X group was scratching at the treatment site 2 days after treatment. Slight cough was noted in 7 different kittens (2-0X, 2-1X, and 3-5X) during the 13-day period following the first treatment. Histopathology showed granulomatous inflammation at the treatment site in three 1X kittens. Causal relationship to the drug could not be determined. Pulmonary inflammation (1-5X) and lymphoid hyperplasia (2-1X, 4-3X) were seen in treated kittens. In a second study, Advantage Multi for Cats was topically applied at 0, 1.7, 5.2 and 8.7X the maximum dose to 48 healthy 9-week-old kittens every two weeks for 6 doses. One kitten in the 8.7X group apparently ingested an unknown amount of the drug and developed the following clinical signs prior to euthanasia: mydriasis, salivation, depression, vomiting, unsteadiness, rapid to slow to difficult breathing, poor pupillary response, generalized tremors, inability to move, and nystagmus. Two kittens in the 5.2X group developed mydriasis, salivation, depression, squinting, and poor appetite. A kitten in the 1.7X group developed mydriasis.

Dose Tolerance Study: Eight healthy juvenile cats were topically dosed with a single application of Advantage Multi for Cats at 10 times the recommended dose volume. Mild, transient hypersalivation occurred in two of the cats.

Oral Study in Cats: The oral safety of Advantage Multi for Cats was tested in case of accidental oral ingestion. The maximum topical dose was orally administered to twelve healthy 9-week-old kittens. Hypersalivation (8 of 12 kittens) and vomiting (12 of 12 kittens) were observed immediately post-treatment. Tremors developed in one kitten within 1 hour, resolving without treatment within the next hour. All 12 kittens were either anorexic or had decreased appetite for at least 1 day following treatment. In 3 kittens, the anorexia or decreased appetite continued into the second week following treatment. There was a post-treatment loss of body weight in treated kittens compared to control kittens. In a pilot safety study using kittens younger in age and lighter in weight than allowed by product labeling, an 8-week old kitten weighing 0.6 kg orally received 2X of the label topical dose (0.46 mL/kg). Immediately after dosing, it vomited, had labored breathing and slight tremors. Within 4 hours, it was normal, but was found dead on day 6. Necropsy could not determine the cause of death.

Study in Heartworm Positive Cats: Young adult cats were inoculated subcutaneously with third-stage D. immitis larvae. At 243–245 days post-infection, immunoserology and echocardiography were performed to identify cats with adult heartworm burdens similar to naturally-acquired infections. Two groups were treated topically with either Advantage Multi for Cats at the label dose or placebo, once every 28 days, for three consecutive treatments. A third group was treated topically, once, with Advantage Multi for Cats at 5X the label dose. Sporadic vomiting and labored breathing related to heartworm burden were observed in the treatment and control groups. There was no difference between treatment groups in the numbers of adult D. immitis recovered at study conclusion. No adverse reactions were associated with the topical application of Advantage Multi for Cats to experimentally heartworm-infected cats.

FERRETS

Use only the 0.4 mL ADVANTAGE MULTI for Cats in ferrets. The 0.23 mL size does not provide an effective dose and the 0.8mL size could result in an overdose.

INDICATIONS:

For ferrets:

Advantage Multi for Cats is indicated for the prevention of heartworm disease in ferrets caused by Dirofilaria immitis. Advantage Multi for Cats kills adult fleas (Ctenocephalides felis) and is indicated for the treatment of flea infestations on ferrets.

WARNINGS:

Do not use on sick or debilitated ferrets.

PRECAUTIONS:

Do not dispense dose applicator tubes without complete safety and administration information.

The safety of Advantage Multi for Cats has not been established in breeding, pregnant, and lactating ferrets.

Treatment of ferrets weighing less than 2.0 lbs (0.9 kg) should be based on a risk-benefit assessment.

The effectiveness of Advantage Multi for Cats in ferrets weighing over 4.4 lbs (2.0 kg) has not been established.

ADVERSE REACTIONS:

Field Safety Study in Ferrets: Advantage Multi for Cats was topically administered to 131 client-owned ferrets at the recommended dose volume (0.4 mL). The ferrets ranged in age from 3 months to 7 years, and weighed between 0.5 and 1.86 kg (1.1 to 4.1 lbs). The dose of imidacloprid ranged between 21.5 to 80.2 mg/kg in this study. The dose of moxidectin ranged between 2.2 to 8.0 mg/kg in this study.

Adverse reactions in ferrets following treatment included: pruritus/scratching, scabbing, redness, wounds and inflammation at the treatment site; lethargy; and chemical odor. These adverse reactions resolved without additional therapy. Owners also reported stiffening of the hair at the treatment site, however, this is expected with application of a topical product and is not considered an adverse reaction.

Three human adverse reactions were reported. An owner's finger became red following skin contact with the product. One owner reported a headache caused by the chemical odor of the product. One owner reported a tingling sensation of the lips after kissing the treatment site.

Foreign Market Experience: Because the following events were reported voluntarily during post-approval use of the product in foreign markets, it is not always possible to reliably establish a causal relationship to drug exposure. Adverse events reported in ferrets topically treated with 0.4 mL imidacloprid + moxidectin for cats included: malaise, vomiting, diarrhea, shaking, mydriasis, hypersalivation with abnormal neurologic signs, seizures, death, generalized hematoma of the body, and alopecia at the treatment site. Adverse reactions in humans included: burning, tingling, numbness, bad taste in the mouth, dizziness, and headache.

ANIMAL SAFETY:

Ferrets: Advantage Multi for Cats was topically applied at 5X the recommended dose volume to six healthy 9-month-old ferrets on Study Days 0, 14, 28, and 42. Because the weights of the ferrets in this study ranged from 2.0 to 4.0 lb (0.9 kg to 1.8 kg), ferrets received a range of dosages from 51.0 to 106.9 mg/lb (112 to 235 mg/kg) of imidacloprid and 5 to 10.5 mg/lb (11 to 23 mg/kg) of moxidectin. The following abnormal clinical signs were reported during the study: wet, matted, and/or greasy appearance to the hair, shaking of the head and/or body, rubbing of dose site on cage, and shedding. Slight increases in phosphorous, potassium, aspartate aminotransferase (AST), and glucose were seen during the study, however, no clinical signs related to these bloodwork changes were reported.

Oral Safety Study: Advantage Multi for Cats was orally administered at the recommended dose volume (0.4 mL) to eight healthy ferrets on Study Day 0. Ferrets were 78 to 101 days old (11.1 to 14.4 weeks) and weighed between 1.1 to 1.8 lb (0.5 to 0.8 kg) body weight on the day of dosing, resulting in doses ranges of 22.0–36.8 mg/lb (48.3–81.0 mg/kg) imidacloprid and 2.2–3.7 mg/lb (4.8–8.0 mg/kg) moxidectin. The following abnormal clinical signs were reported immediately following oral administration of Advantage Multi for Cats: vomiting (one ferret) and ataxia (two ferrets). All abnormalities resolved without treatment or supportive care.

DOSAGE AND ADMINISTRATION:

For ferrets:

The recommended minimum dose for a ferret is 9 mg/lb (20 mg/kg) imidacloprid and 0.9 mg/lb (2 mg/kg) moxidectin, once a month, by topical administration.

Ferret (lbs.) | Advantage Multi For Cats | Volume (mL) | Imidacloprid (mg) | Moxidectin (mg)
2.0–4.4 | Advantage Multi 9 | 0.4 | 40 | 4

Only the 0.4 mL applicator tube volume (Advantage Multi 9) should be used on ferrets.

Do not apply to irritated skin.

1. Remove one dose applicator tube from the package. Administer the entire contents of the Advantage Multi for Cats tube (0.4 mL).
2. While holding the tube in an upright position, remove the cap from the tube.
3. Turn the cap over and push the other end of cap onto the tip of the tube.
4. Twist the cap to break the seal and then remove cap from the tube.
5. Part the hair on the back of the ferret's neck at the base of the head, until the skin is visible. Place the tip of the tube on the skin and apply the entire contents directly on the exposed skin. Lift tube away from skin before releasing pressure on tube.

Do not get this product in the ferret's mouth or eyes or allow the ferret to lick the application site for 30 minutes. Treatment at the base of the head will minimize the opportunity for ingestion by grooming. In households with multiple pets, keep animals separated to prevent licking of the application site.

Stiff, matted hair or a damp, oily appearance of the hair may be observed at the application site on some ferrets. This is temporary and does not affect the safety or effectiveness of the product.

Heartworm Prevention: For prevention of heartworm disease, Advantage Multi for Cats should be administered at one-month intervals. Advantage Multi for Cats may be administered year-round or at a minimum should start one month before the first expected exposure to mosquitoes and should continue at monthly intervals until one month after the last exposure to mosquitoes. If a dose is missed and a 30-day interval between doses is exceeded, administer Advantage Multi for Cats immediately and resume the monthly dosing schedule.

Flea Treatment: For the treatment of flea infestations on ferrets, Advantage Multi for Cats should be administered at one-month intervals. If the ferret is already infested with fleas when the first dose of Advantage Multi for Cats is administered, adult fleas on the ferret will be killed. However, re-infestation from the emergence of pre-existing pupae in the environment may continue to occur for six weeks or longer after treatment is initiated.

STORAGE INFORMATION:

Store at temperatures between 4 °C (39 °F) and 25 °C (77 °F), avoiding excess heat or cold.

HOW SUPPLIED:

Applications Per Package

3 x 0.23 mL tubes

6 x 0.4 mL tubes

6 x 0.8 mL tubes

PA513355X

Revised: August 2025

Approved by FDA under NADA # 141-254

© 2025 Elanco or its affiliates.

Advantage Multi, Elanco and the diagonal bar logo are trademarks of Elanco or its affiliates.

Product of Germany.

ElancoTM

Manufactured for:
Elanco US Inc
Indianapolis, IN 46221 U.S.A.

Principal Display Panel - 0.23 mL Carton Label

2 –
5 lbs

Heartworm

Fleas

Hookworm

Roundworm

Ear Mites

3 Pack

advantage multi™
for cats

(imidacloprid+moxidectin)

Topical Solution

CAUTION: Federal Law restricts this drug to
use by or on the order of a licensed veterinarian

Once-A-Month Topical Solution

- Prevention of heartworm disease
- Kills adult fleas and is indicated for the treatment of
  flea infestations
- Treatment and control of ear mite infestations
- Treatment and control of hookworms and roundworms
- For cats and kittens 9 weeks of age and older
  and 2 –5 lbs.

Children should not come in contact with
the application site for 30 minutes after application.

Do not use the 0.23 mL size tube in ferrets as it does
not provide an effective dose.

Each tube contains 23 mg of imidacloprid and 2.3 mg
of moxidectin.

Keep this and all drugs out of reach of children.

Approved by FDA under NADA # 141-254

THREE 0.23 mL Tubes

Principal Display Panel - 0.4 mL Carton Label

5.1-
9 lbs

for
cats:

Heartworm

Fleas

Hookworm

Roundworm

Ear Mites

for
ferrets:

Heartworm

Fleas

6 Pack

advantage multi™
for cats

(imidacloprid+moxidectin)

Topical Solution for Cats and Ferrets

CAUTION: Federal Law restricts this drug to
use by or on the order of a licensed veterinarian

Once-A-Month Topical Solution

For Cats:

- Prevention of heartworm disease
- Kills adult fleas and is indicated for the treatment of flea infestations
- Treatment and control of ear mite infestations
- Treatment and control of hookworms and roundworms
- For cats and kittens 9 weeks of age and older and 5.1–9 lbs.

For Ferrets:

- Prevention of heartworm disease
- Kills adult fleas and treats flea infestations
- For ferrets that weigh at least 2 lbs.

Children should not come in contact with
the application site for 30 minutes after application.

Each tube contains 40 mg of imidacloprid and 4 mg of moxidectin.

Keep this and all drugs out of reach of children.

Approved by FDA under NADA # 141-254

SIX 0.4 mL Tubes

Principal Display Panel - 0.8 mL Carton Label

9.1 –
18 lbs

Heartworm

Fleas

Hookworm

Roundworm

Ear Mites

6 Pack

advantage multi™
for cats

(imidacloprid+moxidectin)

Topical Solution

CAUTION: Federal Law restricts this drug to
use by or on the order of a licensed veterinarian

Once-A-Month Topical Solution

- Prevention of heartworm disease
- Kills adult fleas and is indicated for the treatment of
  flea infestations
- Treatment and control of ear mite infestations
- Treatment and control of hookworms and roundworms
- For cats and kittens 9 weeks of age and older
  and 9.1 –18 lbs.

Children should not come in contact with
the application site for 30 minutes after application.

Do not use the 0.8 mL size tube in ferrets as it could
result in an overdose.

Each tube contains 80 mg of imidacloprid and 8 mg
of moxidectin.

Keep this and all drugs out of reach of children.

Approved by FDA under NADA # 141-254

SIX 0.8 mL Tubes